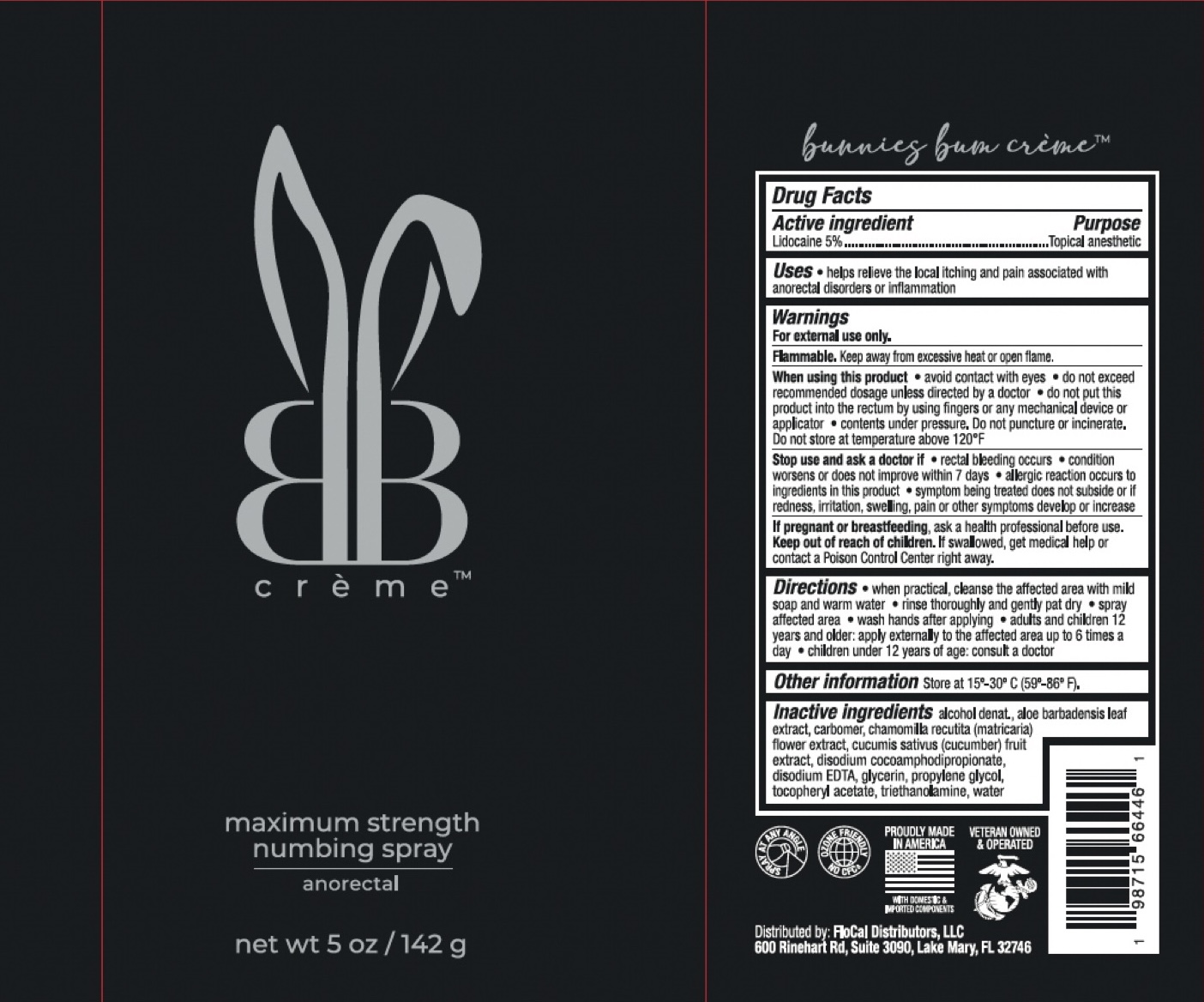 DRUG LABEL: Bunnies Bum Anorectal Numbing
NDC: 84308-173 | Form: SPRAY
Manufacturer: FloCal Distributors LLC
Category: otc | Type: HUMAN OTC DRUG LABEL
Date: 20250608

ACTIVE INGREDIENTS: LIDOCAINE 5 g/100 g
INACTIVE INGREDIENTS: ALCOHOL; CARBOMER 940; ALOE VERA LEAF; .ALPHA.-TOCOPHEROL ACETATE; CHAMOMILE; GLYCERIN; PROPYLENE GLYCOL; CUCUMBER; DISODIUM COCOAMPHODIPROPIONATE; WATER; TROLAMINE; ASCORBIC ACID; EDETATE DISODIUM

ACTIVE INGREDIENT

Lidocaine 5%

PURPOSE

Topical anesthetic

INDICATIONS AND USAGE

Helps relieve the local itching and pain associated with anorectal disorders or inflammation.

WARNINGS

For external use only.

Flammable. Keep away from excessive heat or open flame.

When using this product

- avoid contact with eyes
- do not exceed recommended dosage unless directed by a doctor
- do not put this into the rectum by using fingers or any mechanical device or applicator
- contents under pressure. Do not puncture or incinerate. Do not store at temperature above 120F.

Stop use and ask a doctor if

- rectal bleeding occurs
- condition worsens or does not improve within 7 days
- allergic reaction occurs to ingredients in this product
- symptom being treated does not subside or if redness, irritation, swelling, pain or other symptoms develop or increase

PREGNANCY OR BREAST FEEDING

Ask a health professional before use.

KEEP OUT OF REACH OF CHILDREN

If swallowed, get medical help or contact a Poison Control Center right away.

DOSAGE AND ADMINISTRATION

- When practical, cleanse the affected area with mild soap and warm water, rinse thoroughly and gently pat dry. Spray affected area, wash hands after applying.
- Adults and children 12 years and older: apply externally to the affected area up to 6 times a day
- Children under 12 years of age: consult a doctor.

INACTIVE INGREDIENT

Alcohol denat., aloe barbadensis leaf extract, carbomer, chamomilla recutita (matricaria) flower extract, cucumis sativus (cucumber) fruit extract, disodium cocoamphodipropionate, disodium EDTA, glycerin, propylene glycol, tocopheryl acetate, triethanolamine, water.